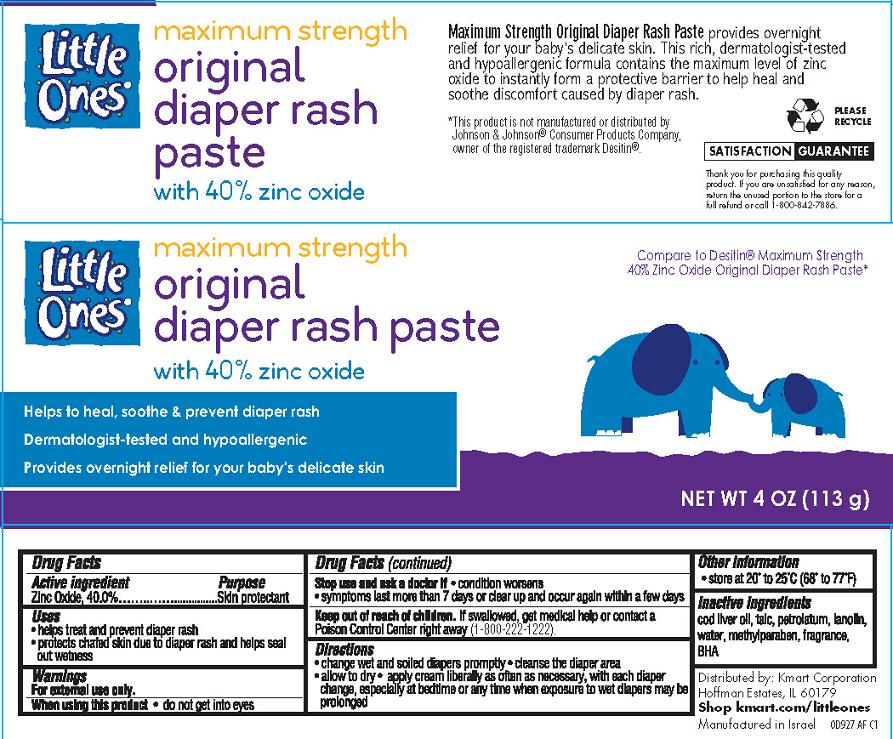 DRUG LABEL: Maximum Strength Original Diaper Rash
NDC: 49738-927 | Form: CREAM
Manufacturer: KMART Corporation
Category: otc | Type: HUMAN OTC DRUG LABEL
Date: 20130923

ACTIVE INGREDIENTS: ZINC OXIDE 400 mg/1 g
INACTIVE INGREDIENTS: COD LIVER OIL; TALC; PETROLATUM; LANOLIN; WATER; METHYLPARABEN; BUTYLATED HYDROXYANISOLE

Little Ones Maximum Strength Original Diaper Paste

Active ingredient

Zinc Oxide........40.0%

Purpose

Skin Protectant

Uses

- helps treat and prevent diaper rash
- protects chafed skin due to diaper rash and helps seal out wetness

Warnings

For external use only.

When using this product

- do not get into eyes

Stop use and ask a doctor if

- condition worsens
- symptoms last more than 7 days or clear up and occur again within a few days

Keep Out of Reach of Children.

If swallowed, get medical help or contact a Poison Control Center right away. (1-800-222-1222)

Directions

- change wet and soiled diapers promptly
- cleanse the diaper area
- allow to dry
- apply cream liberally as often as necessary, with each diaper change, especially at bedtime or any time when exposure to wet diapers may be prolonged

Other Information

- store at 20º to 25ºC (68º to 77ºF)

Inactive ingredients

cod liver oil, talc, petrolatum, lanolin, water, methylparaben, fragrance, BHA

Package/Label Principal Display Panel

Little Ones maximum strength original diaper rash paste

With 40% zinc oxide

Helps to heal, soothe & prevent diaper rash

Dermatologist-tested and hypoallergenic

Provides overnight relief for your baby's delicate skin

Compare to Desitin® Maximum Strength 40% Zinc Oxide Original Diaper Rash Paste*

NET WT. 4 OZ. (113 G)

Maximum Strength Original Diaper Rash Paste provides overnight relief for your baby's delicate skin. This rich, dermatologist-tested and hypoallergenic formula contains the maximum level of zinc oxide to instantly form a protective barrier to help heal and soothe discomfort caused by diaper rash.

SATISFACTION GUARANTEE

Thank you for purchasing this quality product. If you are unsatisfied for any reason, return the unused portion to the store for a full refund or call 1-800-842-7886.

Distributed by: Kmart Corporation
Hoffman Estates, IL 60179
Shop kmart.com/littleones

Manufactured in Israel
0D927 AF C1

*This product is not manufactured or distributed by Johnson & Johnson® Consumer Products Company, owner of the registered trademark Desitin®

Carton Label